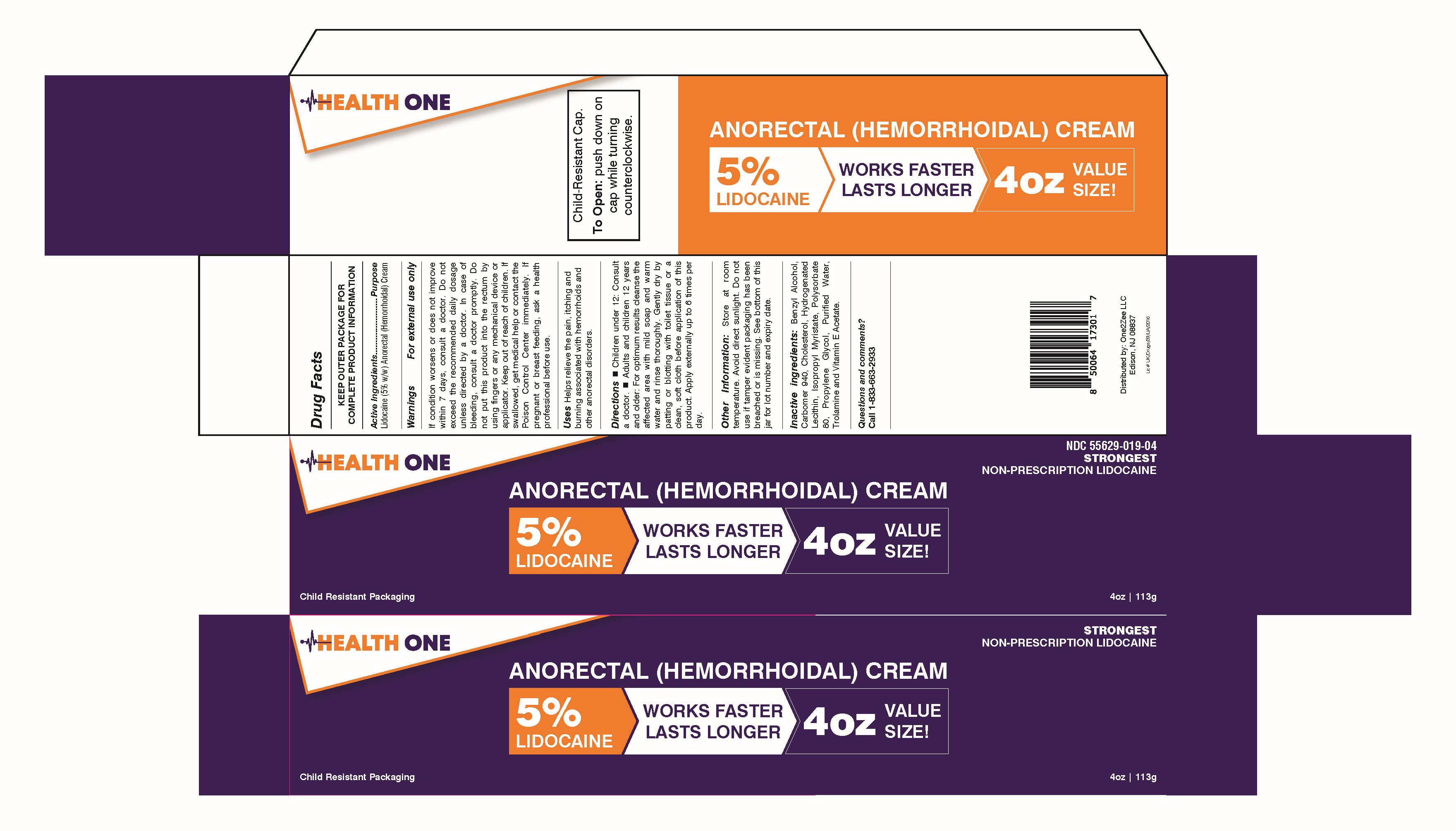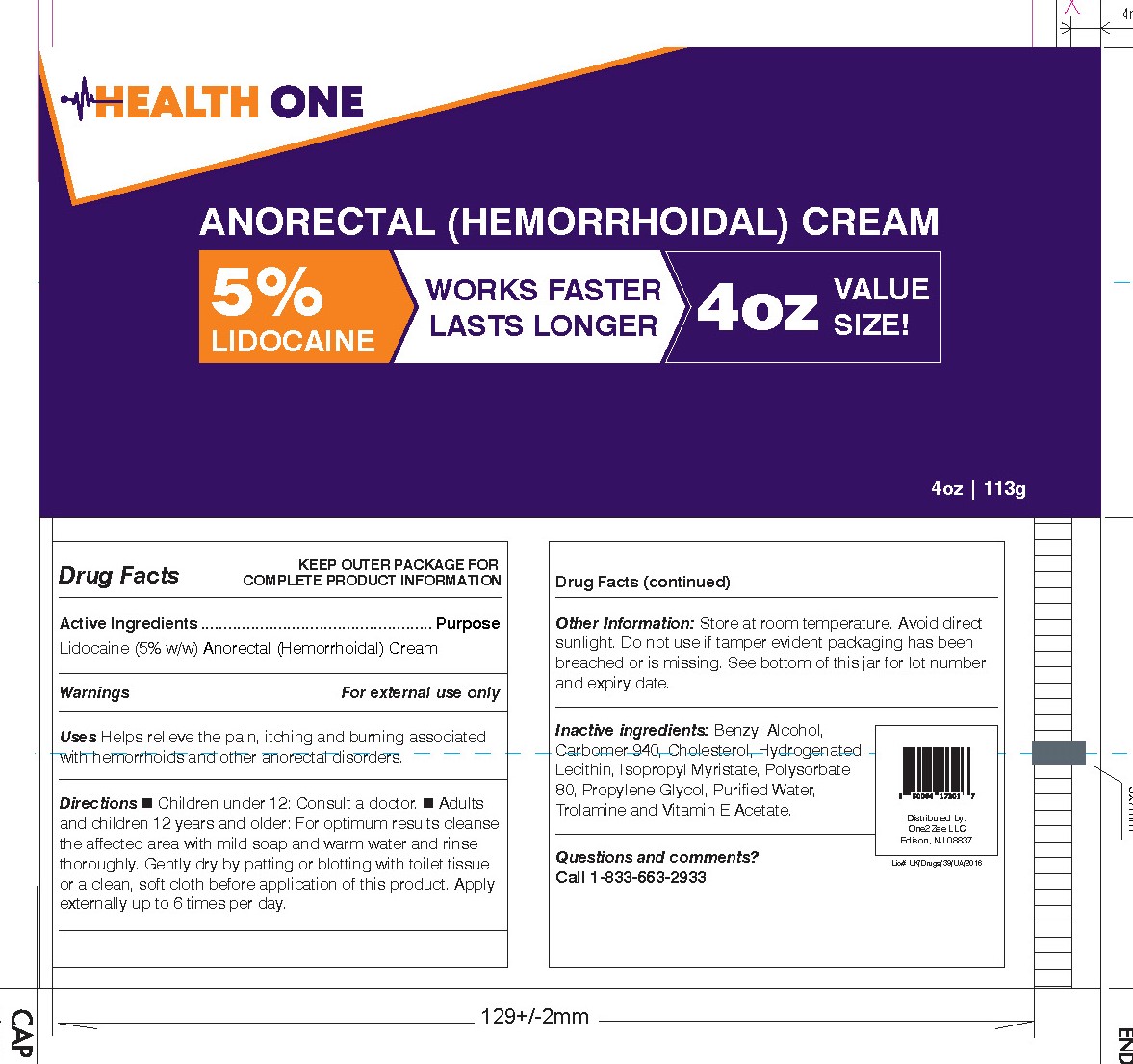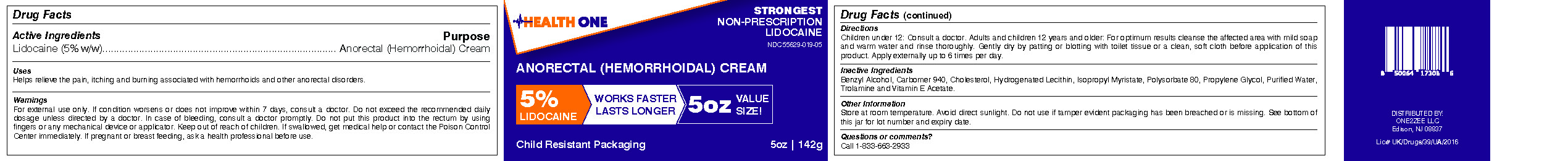 DRUG LABEL: Anorectal Hemorrhoidal Cream with Lidocaine 5%
NDC: 55629-019 | Form: CREAM
Manufacturer: ONE2ZEE LIMITED LIABILITY COMPANY
Category: otc | Type: HUMAN OTC DRUG LABEL
Date: 20240925

ACTIVE INGREDIENTS: LIDOCAINE 0.05 g/1 g
INACTIVE INGREDIENTS: BENZYL ALCOHOL; CARBOMER 940; CHOLESTEROL; LECITHIN, SOYBEAN; ISOPROPYL MYRISTATE; POLYSORBATE 80; PROPYLENE GLYCOL; WATER; TROLAMINE; .ALPHA.-TOCOPHEROL ACETATE

Annorectal (Hemorrhoidal) Cream with Lidocaine 5%

Active Ingredient:

Lidocaine HCl 5.0%

Purpose

- Anorectal (Hemorrhoidal) Cream

Uses:

Helps relieve the pain, itching and burning associated with hemorrhoids and other anorectal disorders.

Warnings:

- For external use only. If condition worsens or does not improve within 7 days, consult a doctor.

When using this product,

- Do not exceed the recommended daily dosage unless directed by a doctor.
- In case of bleeding, consult a doctor promptly.
- Do not put this product into the rectum by using ﬁngers or any mechanical device or applicator.
- Keep out of reach of children.
- If swallowed, get medical help or contact the Poison Control Center immediately.
- If pregnant or breast feeding, ask a health professional before use.

Directions:

Children under 12: Consult a doctor.

Adults and children 12 years and older: For optimum results cleanse the affected area with mild soap and warm water and rinse thoroughly. Gently dry by patting or blotting with toilet tissue or a clean, soft cloth before application of this product. Apply externally up to 6 times per day.

Inactive Ingredients

Benzyl Alcohol, Carbomer 940, Cholesterol, Hydrogenated Lecithin, Isopropyl Myristate, Polysorbate 80, Propylene Glycol, Puriﬁed Water, Trolamine and Vitamin E Acetate

Other Information:

Store at room temperature. Avoid direct sunlight. Do not use if tamper evident packaging has been breached or is missing. See bottom of this jar for lot number and expiry date.

Distributed by: Wellspring Airmont, NY 10952 U.S.A.